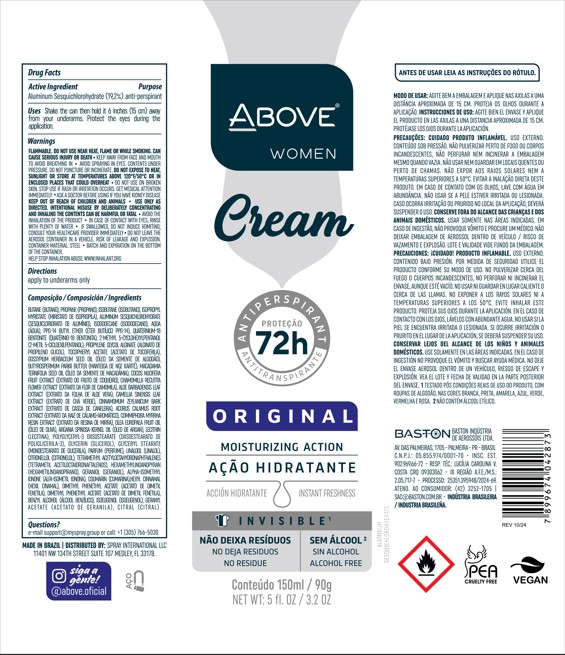 DRUG LABEL: ABOVE  ORIGINAL WOMAN
NDC: 73306-1180 | Form: AEROSOL, SPRAY
Manufacturer: BASTON INDUSTRIA DE AEROSSOIS LTDA
Category: otc | Type: HUMAN OTC DRUG LABEL
Date: 20250225

ACTIVE INGREDIENTS: ALUMINUM SESQUICHLOROHYDRATE 19.2 g/90 g
INACTIVE INGREDIENTS: ISOBUTANE

ABOVE CREAM ORIGINAL WOMAN ANTIPERSPIRANT DEODORANT 72H SPRAY

ACTIVE INGREDIENT

ALUMINUM SESQUICHOLOHYDRATE (SESQUICLORIDRATO DE ALUMÍNIO)

PURPOSE

UNDERARM ANTIPERSPIRANT DEODORANT

WARNINGS AND PRECAUTIONS

For external use only. Do not use on broken skin. Ask a doctor before use if you have kidney disease. Stop use if rash or irritation occurs. Keep out of reach of children. If swallowed, get medical help or contact a Poison Control Center right away.

WARNINGS

For external use only. Do not use on broken skin. Ask a doctor before use if you have kidney disease. Stop use if rash or irritation occurs. Keep out of reach of children. If swallowed, get medical help or contact a Poison Control Center right away.

INACTIVE INGREDIENT

BUTANE (BUTANO)
PROPANE (PROPANO)
ISOBUTANE (ISOBUTANO)
ISOPROPYL MYRISTATE (MIRISTATO DE ISOPROPILA)
ISODODECANE
PARFUM (PERFUME)
AQUA (ÁGUA)
PPG-14 BUTYL ETHER (ÉTER BUTÍLICO PPG-14)
QUATERNIUM-18 BENTONITE
2-METHYL 5-CYCLOHEXYLPENTANOL (2-METIL 5-CICLOEXILPENTANOL)
PROPYLENE GLYCOL ALGINATE
TOCOPHERYL ACETATE
GOSSYPIUM HERBACEUM SEED OIL (ÓLEO DA SEMENTE DE ALGODÃO)
BUTYROSPERMUM PARKII BUTTER (MANTEIGA DE NOZ KARITÉ)
MACADAMIA TERNIFOLIA SEED OIL (ÓLEO DA SEMENTE DE MACADÂMIA)
COCOS NUCIFERA FRUIT EXTRACT (EXTRATO OLEOSO DE CÔCO)
CHAMOMILLA RECUTITA FLOWER EXTRACT (EXTRATO DA FLOR DE CAMOMILA)
ALOE BARBADENSIS LEAF EXTRACT (EXTRATO DA FOLHA DE ALOE VERA)
CAMELLIA SINENSIS LEAF EXTRACT (EXTRATO DE CHÁ VERDE)
CINNAMOMUM ZEYLANICUM BARK EXTRACT (EXTRATO
ACORUS CALAMUS ROOT EXTRACT
COMMIPHORA MYRRHA RESIN EXTRACT (EXTRATO DA RESINA DE MIRRA)
OLEA EUROPAEA FRUIT OIL (ÓLEO DE OLIVA)
ARGANIA SPINOSA KERNEL OIL (ÓLEO DE ARGAN)
LECITHIN (LECITINA)
POLYGLYCERYL-3 DIISOSTEARATE
GLYCERIN (GLICEROL)
GLYCERYL STEARATE (MONOESTEARATO DE GLICERILA)

QUESTIONS

MAIL : SUPPORT@MYSPRAY.GROUP OR CALL (305) 766-5030 [OTC - QUESTIONS SECTION]

KEEP OUT OF REACH OF CHILDREN

DOSAGE AND ADMINISTRATION

apply to the armpits as much as you think is enough. apply only to the armpits

INDICATIONS AND USAGE

Use on axilas
Do not apply to wet skin
Wait until dry to get dressed